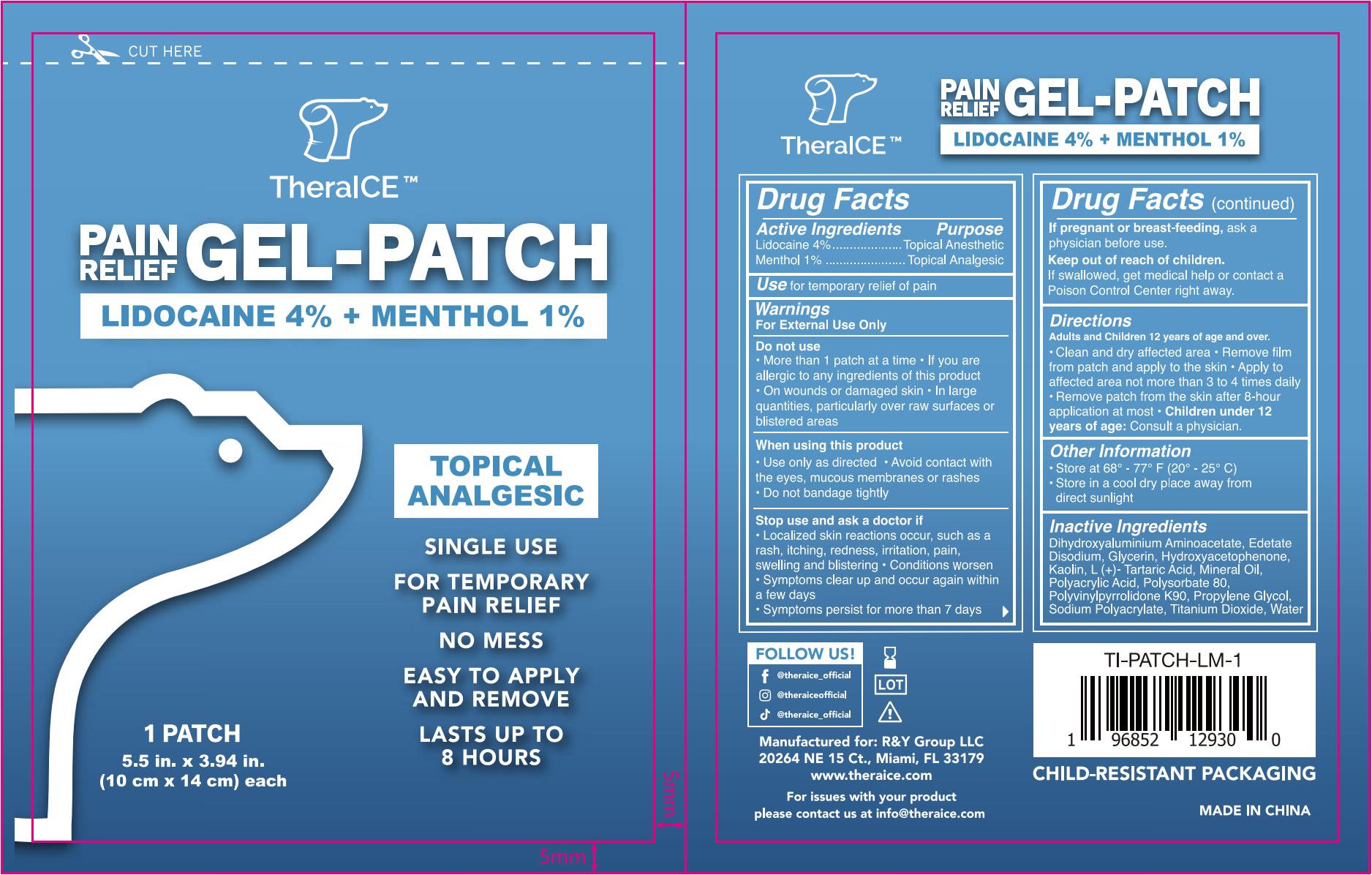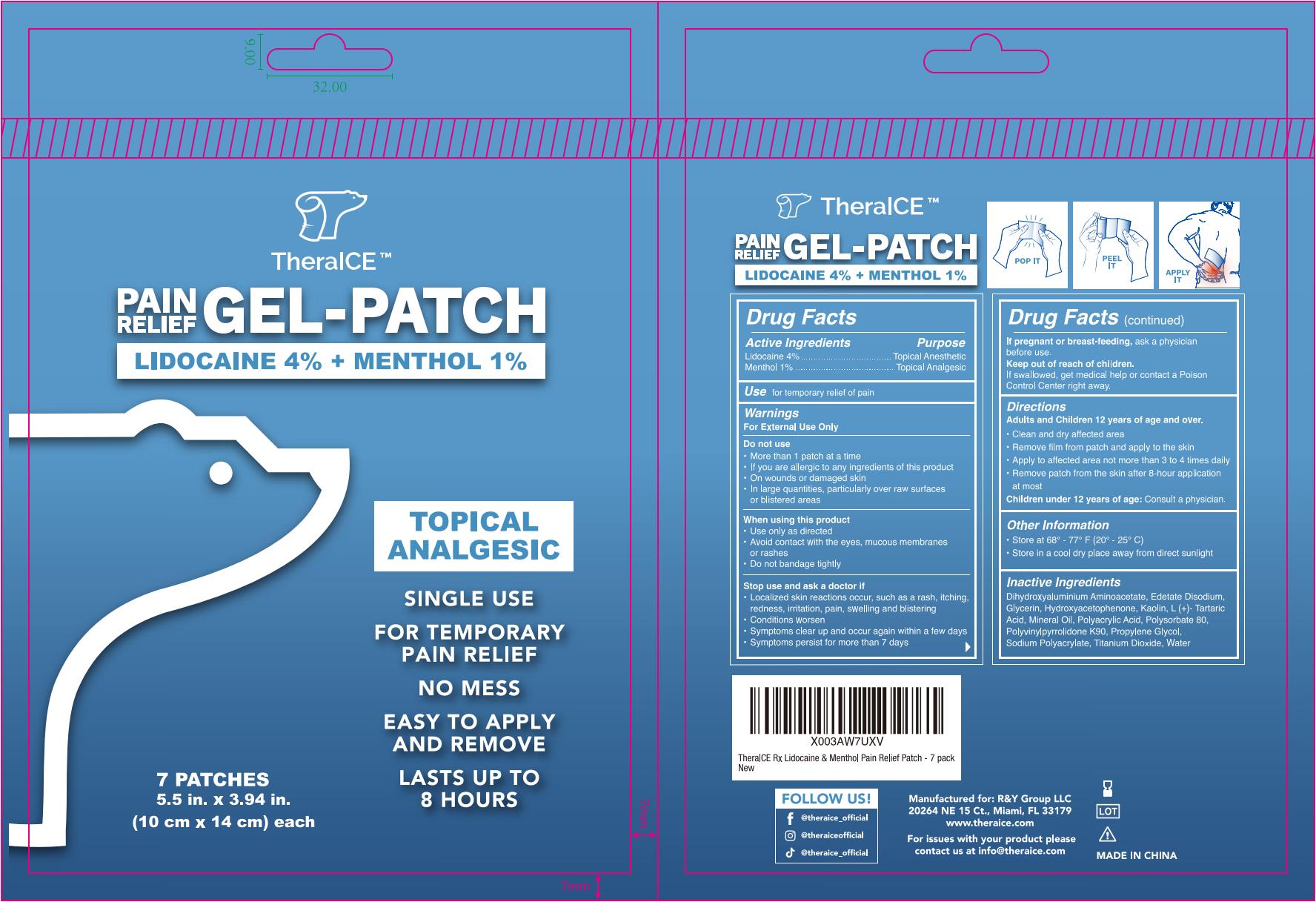 DRUG LABEL: Pain Relief Gel-Patch
NDC: 83016-171 | Form: PATCH
Manufacturer: R & Y Group, LLC
Category: otc | Type: HUMAN OTC DRUG LABEL
Date: 20241030

ACTIVE INGREDIENTS: MENTHOL 0.12 g/12 g; LIDOCAINE 0.48 g/12 g
INACTIVE INGREDIENTS: KAOLIN; TARTARIC ACID; WATER; DIHYDROXYALUMINUM AMINOACETATE ANHYDROUS; PROPYLENE GLYCOL; POLYACRYLIC ACID (250000 MW); SODIUM POLYACRYLATE (2500000 MW); TITANIUM DIOXIDE; MINERAL OIL; POLYSORBATE 80; GLYCERIN; EDETATE DISODIUM; POVIDONE K90; HYDROXYACETOPHENONE

TheraICETM Lidocaine&Menthol Pain Relief Gel-Patch, 7 Patches

Active Ingredients

Lidocaine 4% w/w ...... Purpose: Topical Anesthetic

Menthol 1% w/w ...... Purpose: Topical Analgesic

Purpose

Topical Anesthetic (Lidocaine)

Topical Analgesic (Menthol)

Use

for temporary relief of pain

Warnings

For External Use Only

Do not use

- More than 1 patch at a time
- If you are allergic to any ingredients of this product
- On wounds or damaged skin
- In large quantities, particularly over raw surfaces or blistered areas

When using this product

- Use only as directed
- Avoid contact with the eyes, mucous membranes or rashes
- Do not bandage tightly

Stop use and consult a doctor if

- Localized skin reactions occur, such as a rash, itching, redness, irritation, pain, swelling and blistering
- Conditions worsen
- Symptoms clear up and occur again within a few days
- Symptoms persist for more than 7 days

If pregnant or breast-feeding,

ask a physician before use.

Keep out of reach of children.

If swallowed, get medical help or contact a Poison Control Center right away.

Directions

Adults and Children 12 years of age and over.

- Clean and dry affected area
- Remove film from patch and apply to the skin
- Apply to affected area not more than 3 to 4 times daily
- Remove patch from the skin after 8-hour application at most

Children under 12 years of age: Consult a physician

Other Information

- Store at 68° - 77° F (20° - 25° C)
- Store in a cool dry place away from direct sunlight

Inactive Ingredients

Dihydroxyaluminium Aminoacetate, Edetate Disodium, Glycerin, Hydroxyacetophenone, Kaolin, L(+)-Tartaric Acid, Mineral Oil, Polyacrylic Acid, Polysorbate 80, Polyvinylpyrrolidone K90, Propylene Glycol, Sodium Polyacrylate, Titanium Dioxide, Water